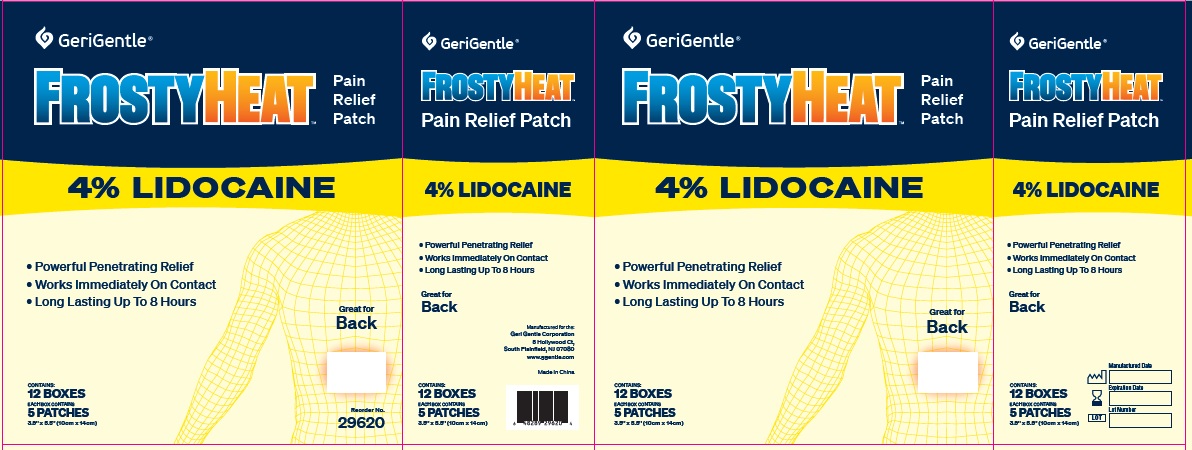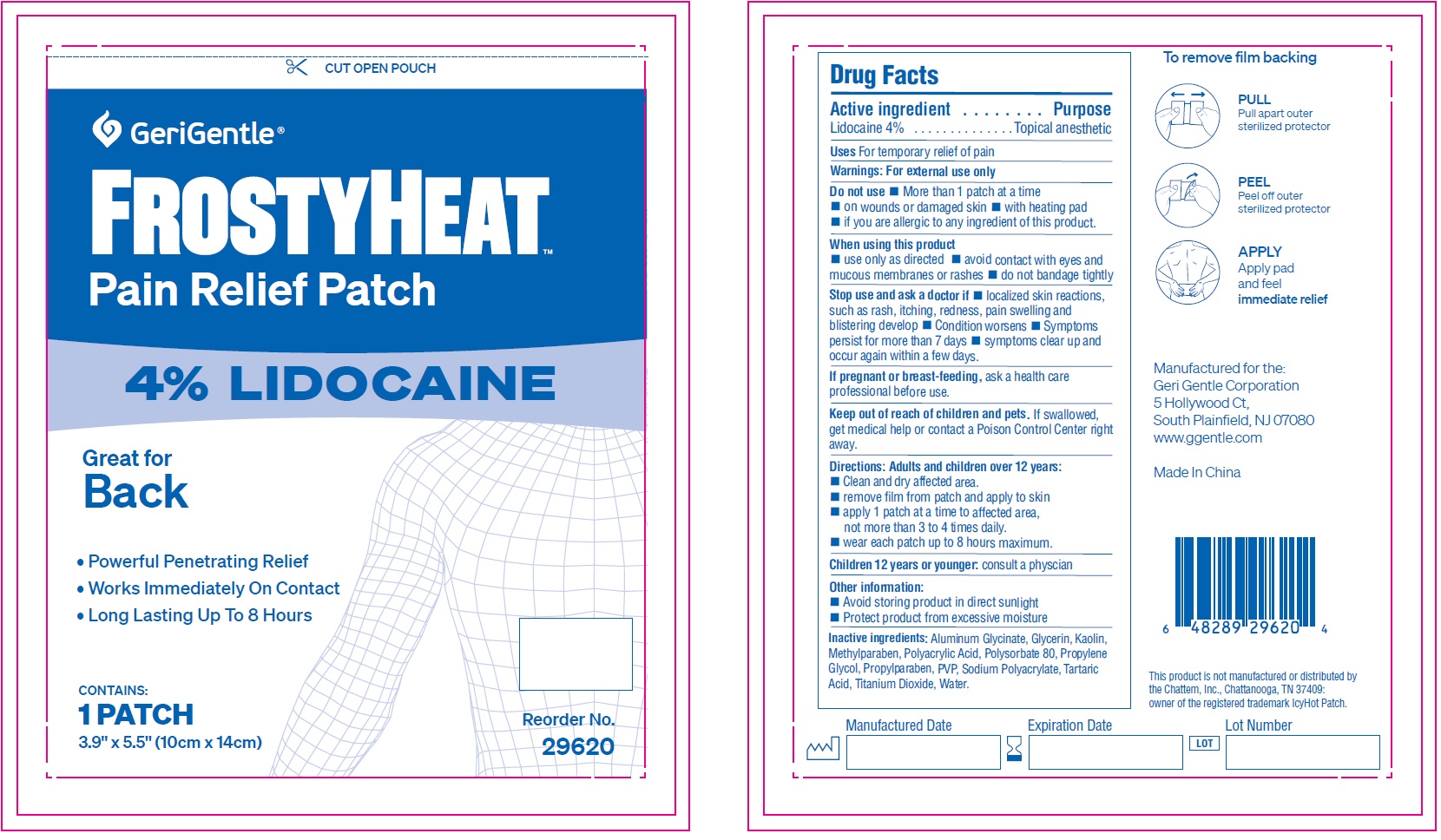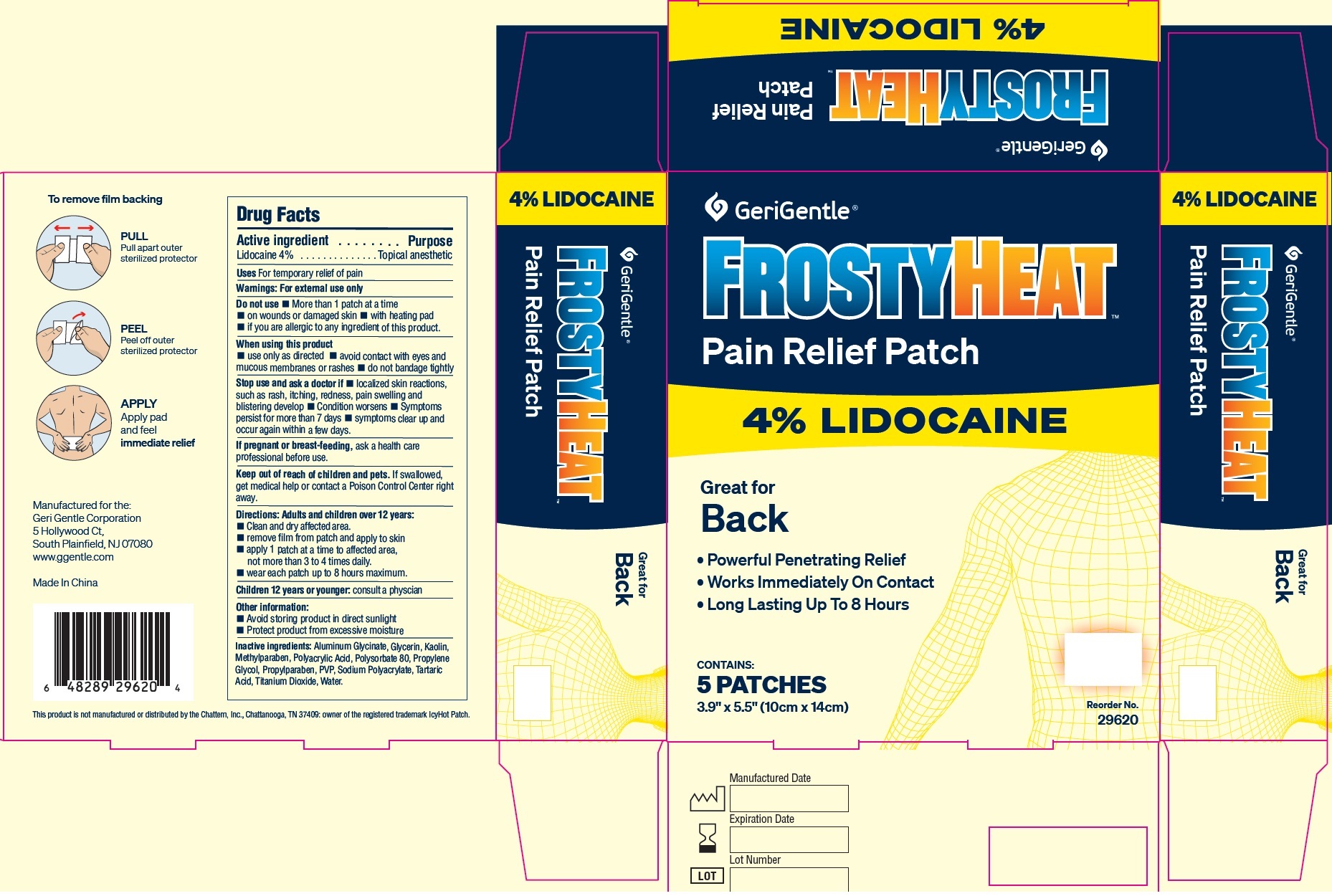 DRUG LABEL: GeriGentle FrostyHeat Pain Relief Patch 4 Lodocaine Back
NDC: 69771-010 | Form: PATCH
Manufacturer: Geri-Gentle Corporation
Category: otc | Type: HUMAN OTC DRUG LABEL
Date: 20231110

ACTIVE INGREDIENTS: LIDOCAINE 40 mg/1 mL
INACTIVE INGREDIENTS: DIHYDROXYALUMINUM AMINOACETATE ANHYDROUS; GLYCERIN; KAOLIN; METHYLPARABEN; POLYSORBATE 80; PROPYLENE GLYCOL; PROPYLPARABEN; POVIDONE, UNSPECIFIED; TARTARIC ACID; TITANIUM DIOXIDE; WATER

GeriGentle FrostyHeat Pain Relief Patch 4% Lodocaine Back

Active ingredient

Lidocaine 4%

Purpose

Topical anesthetic

Uses

For temporary relief of pain

Warnings:

For external use only

Do not use

- More than 1 patch at a time
- on wounds or damaged skin
- with heating pad
- if you are allergic to any ingredient of this product.

When using this product

- use only as directed
- avoid contact with eyes and mucous membranes or rashes
- do not bandage tightly

Stop use and ask a doctor if

- localized skin reactions, such as rash, itching, redness, pain swelling and blistering develop
- Condition worsens
- Symptoms persist for more than 7 days
- symptoms clear up and occur again within a few days.

If pregnant or breast-feeding,

ask a health care professional before use.

Keep out of reach of children and pets.

If swallowed, get medical help or contact a Poison Control Center right away.

Directions:

Adults and children over 12 years:

- Clean and dry affected area.
- remove film from patch and apply to skin
- apply 1 patch at a time to affected area, not more than 3 to 4 times daily.
- wear each patch up to 8 hours maximum.
- consult a physcian Children 12 years or younger:

Other information:

- Avoid storing product in direct sunlight
- Protect product from excessive moisture

Inactive ingredients:

Aluminum Glycinate, Glycerin, Kaolin, Methylparaben, Polyacrylic Acid, Polysorbate 80, Propylene Glycol, Propylparaben, PVP, Sodium Polyacrylate, Tartaric Acid, Titanium Dioxide, Water.